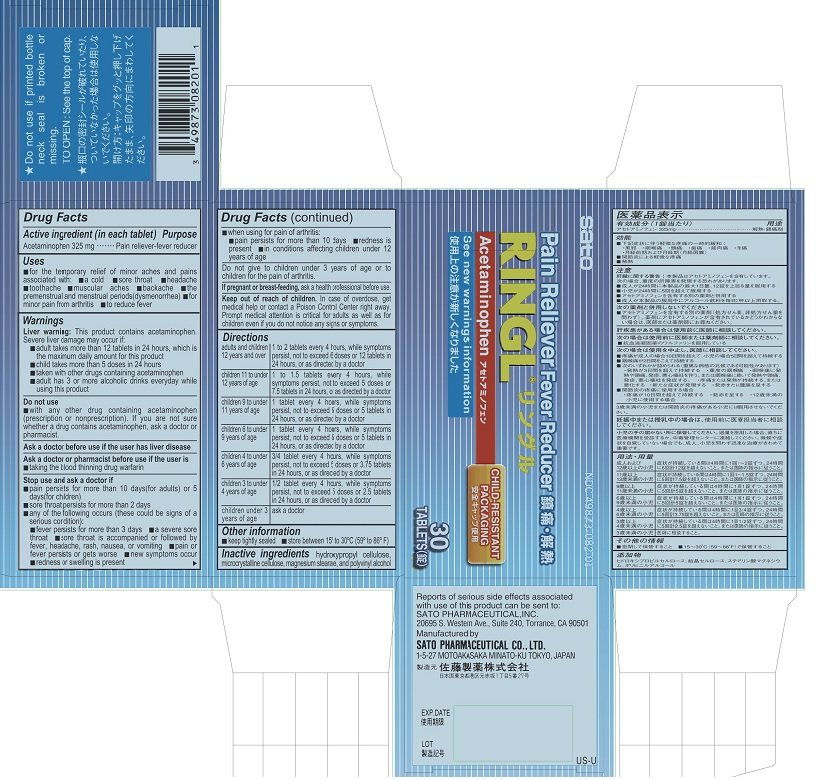 DRUG LABEL: Ringl
NDC: 49873-082 | Form: TABLET
Manufacturer: Sato Pharmaceutical Co., Ltd.
Category: otc | Type: HUMAN OTC DRUG LABEL
Date: 20231206

ACTIVE INGREDIENTS: ACETAMINOPHEN 325 mg/1 1
INACTIVE INGREDIENTS: HYDROXYPROPYL CELLULOSE, LOW SUBSTITUTED; CELLULOSE, MICROCRYSTALLINE; MAGNESIUM STEARATE; POLYVINYL ALCOHOL

Ringl Tablet (final packaged product)

Active ingredient (in each tablet)
Acetaminophen 325 mg

Purpose Pain reliever-fever reducer

Uses
■ for the temporary relief of minor aches and pains associated with:
■ a cold ■ sore throat ■ headache ■ toothache ■ muscular aches
■ backache ■ the premenstrual and menstrual periods (dysmenorrhea)
■ for minor pain from arthritis
■ to reduce fever

Warnings
Liver warning: This product contains acetaminophen. Severe liver damage may occur if:
■ adult takes more than 12 tablets in 24 hours, which is the maximum daily amount for this product
■ child takes more than 5 doses in 24 hours
■ taken with other drugs containing acetaminophen
■ adult has 3 or more alcoholic drinks everyday while using this product

Do not use
■ with any other drug containing acetaminophen (prescription or nonprescription). If you are not sure whether a drug contains acetaminophen, ask a doctor or pharmacist.

Ask a doctor before use if the user has liver disease

Ask a doctor or pharmacist before use if the user is
■ taking the blood thinning drug warfarin

Stop use and ask a doctor if
■ pain persists for more than 10 days (for adults) or 5 days (for children)
■ sore throat persists for more than 2 days
■ any of the following occurs (these could be signs of a serious condition):
■ fever persists for more than 3 days ■ a severe sore throat
■ sore throat is accompanied or followed by fever, headache, rash, nausea, or vomiting
■ pain or fever persists or gets worse ■ new symptoms occur
■ redness or swelling is present
■ when using for pain or arthritis:
■ pain persists for more than 10 days ■ redness is present
■ in conditions affecting children under 12 years of age

PEDIATRIC USE

Do not give to children under 3 years of age or to children for the pain of arthritis.

PREGNANCY OR BREAST FEEDING

If pregnant or breast-feeding, ask a health professional before use.

Keep out of reach of children. In case of overdose, get medical help or contact a Poison Control Center right away. Prompt medical attention is critical for adults as well as for children even if you do not notice any signs or symptoms.

Directions
adults and children 12 years and over: 1 to 2 tablets every 4 hours, while symptoms persist, not to exceed 6 doses or 12 tablets in 24 hours, or as directed by a doctor
children 11 to under 12 years of age: 1 to 1.5 tablets every 4 hours, while symptoms persist, not to exceed 5 doses or 7.5 tablets in 24 hours, or as directed by a doctor
children 9 to under 11 years of age: 1 tablet every 4 hours, while symptoms persist, not to exceed 5 doses or 5 tablets in 24 hours, or as directed by a doctor
children 6 to under 9 years of age: 1 tablet every 4 hours, while symptoms persist, not to exceed 5 doses or 5 tablets in 24 hours, or as directed by a doctor
children 4 to under 6 years of age: 3/4 tablet every 4 hours, while symptoms persist, not to exceed 5 doses or 3.75 tablets in 24 hours, or as directed by a doctor
children 3 to under 4 years of age: 1/2 tablet every 4 hours, while symptoms persist, not to exceed 5 doses or 2.5 tablets in 24 hours, or as directed by a doctor
children under 3 years of age: ask a doctor

Other information
■ keep tightly sealed ■ store between 15° to 30°C (59° to 86° F)

INACTIVE INGREDIENT

Inactive ingredients hydroxypropyl cellulose, microcrystalline cellulose, magnesium stearate, and polyvinyl alcohol.